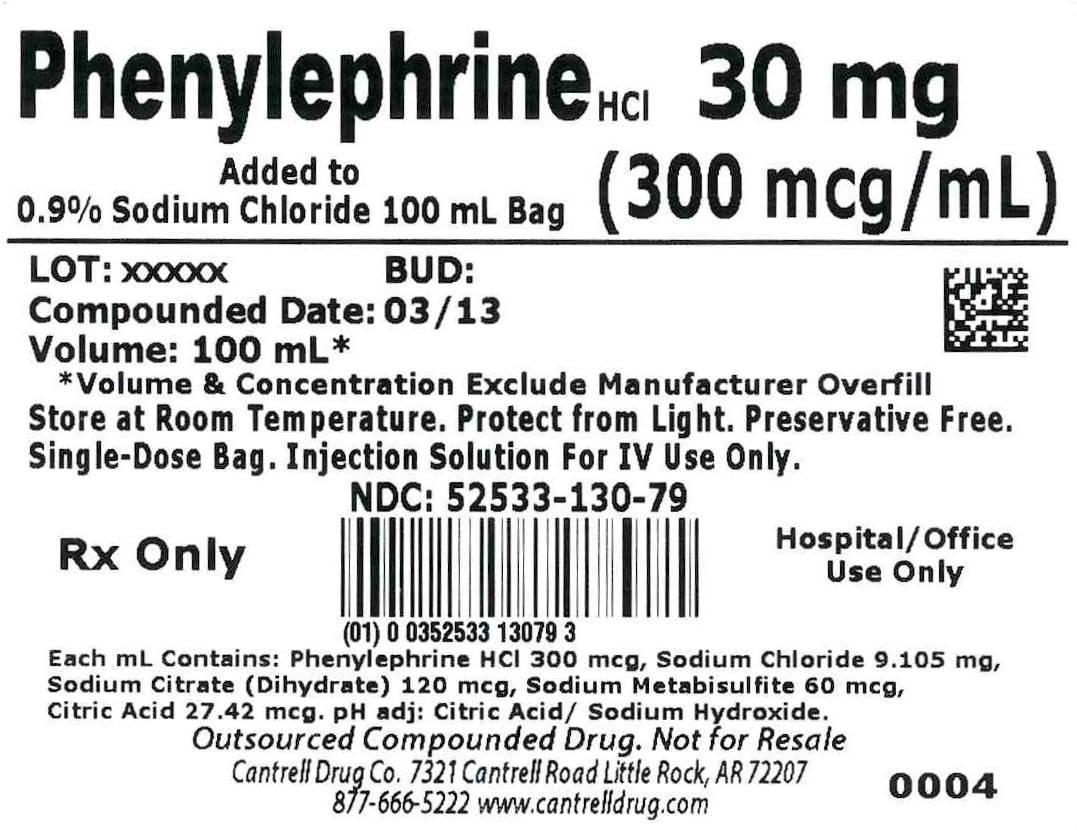 DRUG LABEL: Phenylephrine HCl
NDC: 52533-130 | Form: INJECTION, SOLUTION
Manufacturer: Cantrell Drug Company
Category: prescription | Type: HUMAN PRESCRIPTION DRUG LABEL
Date: 20150112

ACTIVE INGREDIENTS: Phenylephrine Hydrochloride 300 ug/1 mL
INACTIVE INGREDIENTS: Sodium Chloride 9.105 mg/1 mL; TRISODIUM CITRATE DIHYDRATE 120 ug/1 mL; SODIUM METABISULFITE 60 ug/1 mL; CITRIC ACID MONOHYDRATE 27.42 ug/1 mL; WATER

Phenylephrine HCl 30 mg Added to 0.9% Sodium Chloride 100 mL Bag